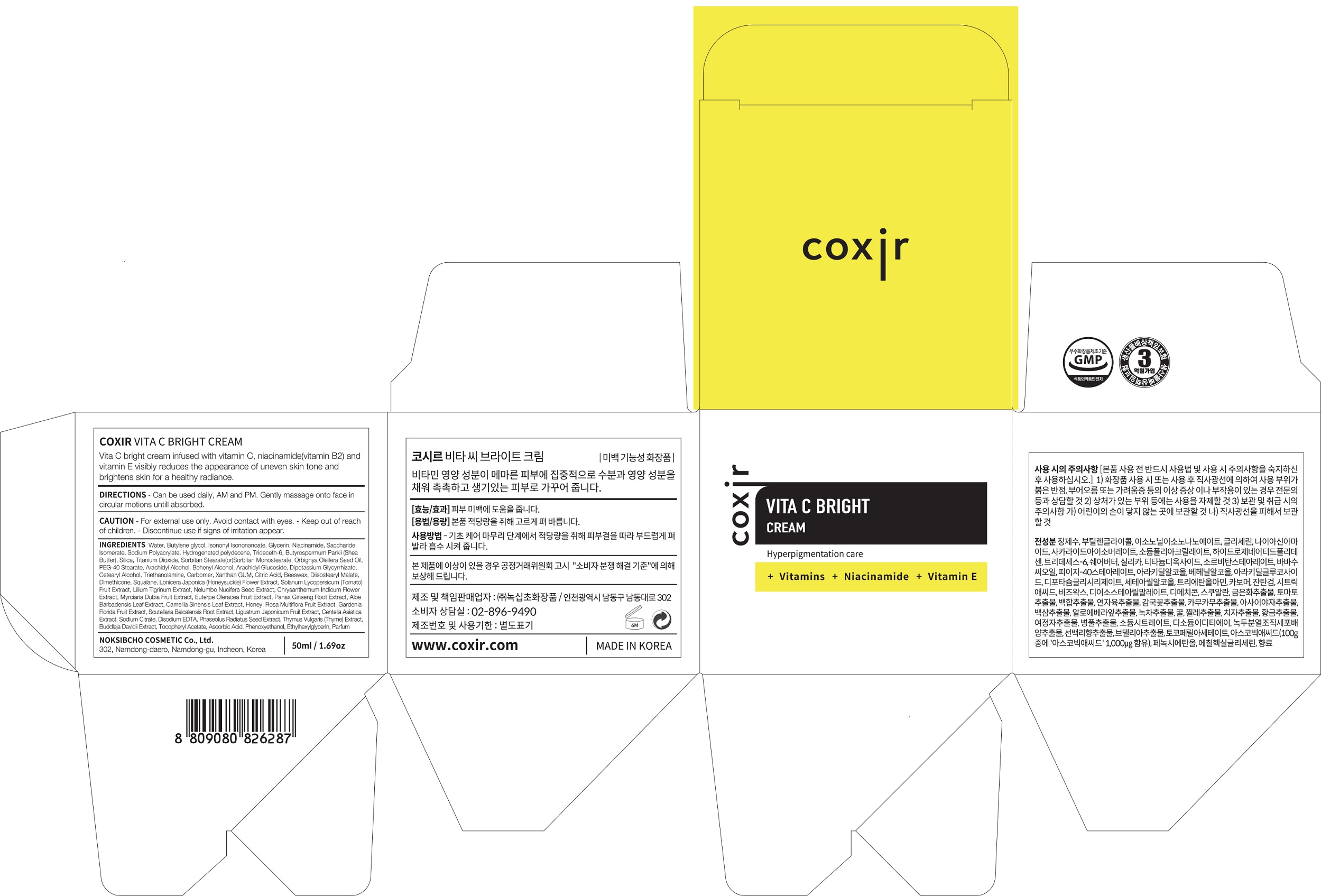 DRUG LABEL: VITA C BRIGHTCREAM
NDC: 73590-0015 | Form: CREAM
Manufacturer: NOKSIBCHO cosmetic Co., Ltd.
Category: otc | Type: HUMAN OTC DRUG LABEL
Date: 20200314

ACTIVE INGREDIENTS: NIACINAMIDE 2 g/100 mL
INACTIVE INGREDIENTS: WATER; BUTYLENE GLYCOL

Drug Facts

ACTIVE INGREDIENT

adenosine, vitamins, vitamin E

INACTIVE INGREDIENT

Water
Butylene glycol
Isononyl Isononanoate
Glycerin
Niacinamide
Saccharide Isomerate
Sodium Polyacrylate
Hydrogenated polydecene
Trideceth-6
Butyrospermum Parkii (Shea Butter)
Silica
Titanium Dioxide
Sorbitan Stearate(or)Sorbitan Monostearate
Orbignya Oleifera Seed Oil
PEG-40 Stearate
Arachidyl Alcohol
Behenyl Alcohol
Arachidyl Glucoside
Dipotassium Glycyrrhizate
Cetearyl Alcohol
Triethanolamine
Carbomer
Xanthan GUM
Citric Acid
Beeswax
Diisostearyl Malate
Dimethicone
Squalane
Lonicera Japonica (Honeysuckle) Flower Extract
Solanum Lycopersicum (Tomato) Fruit Extract
Lilium Tigrinum Extract
Nelumbo Nucifera Seed Extract Chrysanthemum Indicum Flower Extract
Myrciaria Dubia Fruit Extract
Euterpe Oleracea Fruit Extract
Panax Ginseng Root Extract
Aloe Barbadensis Leaf Extract
Camellia Sinensis Leaf Extract
Honey
Rosa Multiflora Fruit Extract
Gardenia Florida Fruit Extract
Scutellaria Baicalensis Root Extract
Ligustrum Japonicum Fruit Extract
Centella Asiatica Extract
Sodium Citrate
Disodium EDTA
Phaseolus Radiatus Meristem Cell Culture Extract
Camellia Sinensis Callus Culture Extract
Thymus Vulgaris (Thyme) Extract
Buddleja Davidii Extract
Tocopheryl Acetate
Ascorbic Acid
Phenoxyethanol
Ethylhexylglycerin
Parfum

PURPOSE

hyperpigmentation care

keep out of reach of the children

INDICATIONS AND USAGE

apply proper amount and gently massage

WARNINGS

For external use only
When using this product

■ if the following symptoms occurs after use, stop use and consult with a skin specialist

red specks, swelling, itching

■ don’t use on the part where there is injury, eczema, or dermatitis

Keep out of reach of children

■ if swallowed, get medical help or contact a person control center immediately

DOSAGE AND ADMINISTRATION

for external use only